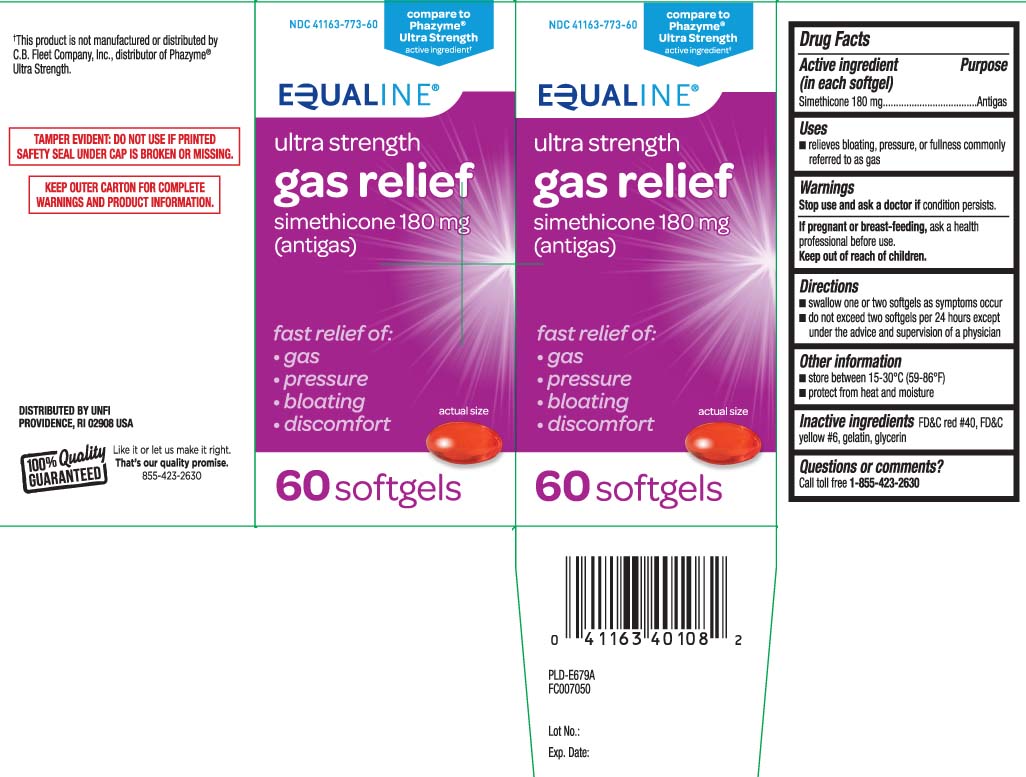 DRUG LABEL: Gas Relief
NDC: 41163-773 | Form: CAPSULE, LIQUID FILLED
Manufacturer: United Natural Foods, Inc. dba UNFI
Category: otc | Type: HUMAN OTC DRUG LABEL
Date: 20240802

ACTIVE INGREDIENTS: DIMETHICONE 180 mg/1 1
INACTIVE INGREDIENTS: FD&C YELLOW NO. 6; GELATIN; GLYCERIN; FD&C RED NO. 40

Drug Facts

Active ingredient (in each softgel)

Simethicone 180 mg

Purpose

Antiflatulent (Antigas)

Uses

- relieves bloating, pressure, or fullness commonly referred to as gas

Warnings

Stop use and ask a doctor if

condition persists.

If pregnant or breast-feeding,

ask a health professional before use.

Directions

- swalow one or two softgels as needed after a meal
- do not exceed two softgels per day except under the advice and supervision of a physician

Other information

- store at 15º-30ºC (59º-86ºF)
- protect from heat and moisture

Inactive ingredients

FD&C red #40, FD&C yellow #6, gelatin, glycerin

Questions or comments?

Call toll free 1-855-423-2630

Principal Display Panel

Compare to Phazyme® Ultra Strength active ingredient†

Ultra Strength

Gas Relief

simethicone 180 mg (antigas)

fast relief of:

- gas
- pressure
- bloating
- discomfort

softgels

†This product is not manufactured or distributed by C.B Fleet Company Inc., distributor of Phazyme® Ultra Strength.

TAMPER EVIDENT: DO NOT USE IF PRINTED SAFETY SEAL UNDER CAP IS BROKEN OR MISSING.

KEEP OUTER CARTON FOR COMPLETE WARNINGS AND PRODUCT INFORMATION.

DISTRIBUTED BY UNFI

PROVIDENCE, RI 02908

Product Label

EQUALINE Ultra Strength Gas Relief